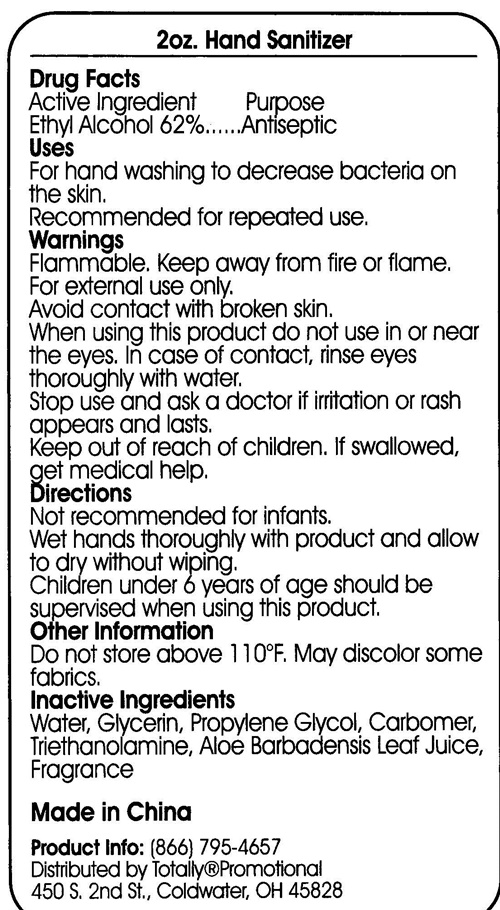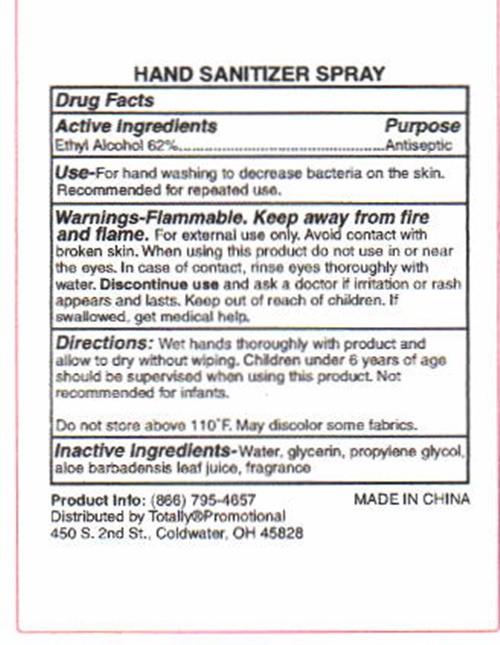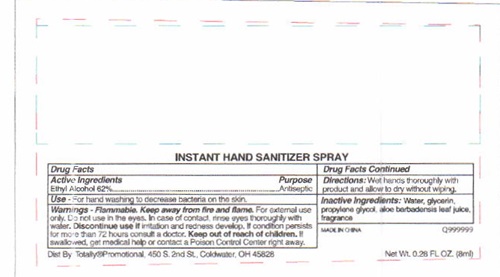 DRUG LABEL: Hand
NDC: 71087-001 | Form: GEL
Manufacturer: CASAD Company, Inc
Category: otc | Type: HUMAN OTC DRUG LABEL
Date: 20250103

ACTIVE INGREDIENTS: ALCOHOL 53.5 g/100 mL
INACTIVE INGREDIENTS: WATER; GLYCERIN; PROPYLENE GLYCOL; CARBOMER 934; TROLAMINE; ALOE VERA LEAF

Hand Sanitizer

Drug Facts Active Ingredient

Ethyl Alcohol 62%

Purpose

Antiseptic

Keep out of reach of children. If swallowed get medical help or contact a Poison Control center right away.

Use

For hand washing to decrease bacteria on the skin. Recommended for repeated use.

Warnings

Flammable. Keep away from fire and flame. For external use only. Avoid contact with broken skin. When using this product do not use in or near the eyes. In case of contact, rinse eyes thoroughly with water. Stop use and ask a doctor if irritation or rash appears and lasts.

Directions

Not recommended for infants. Wet hands thoroughly with product and allow to dry without wiping. Children under 6 years of age should be supervised when using this product

Other Information

Do not store above 110°F. May discolor some fabrics.

Inactive Ingredients

Water, Glycerin, Propylene Glycol, Carbomer, Triethanolamine, Aloe Barbadensis Leaf juise, Fragrance

Hand Sanitizer product label

Hand Sanitizer, INSTANT HAND SANITIZER SPRAY, HAND SANITIZER SPRAY

Made in China

Product Info: (866) 795-4657
Distributed by Totally®Promotional
450 S. 2nd Sr., Coldwater, OH 45828

res